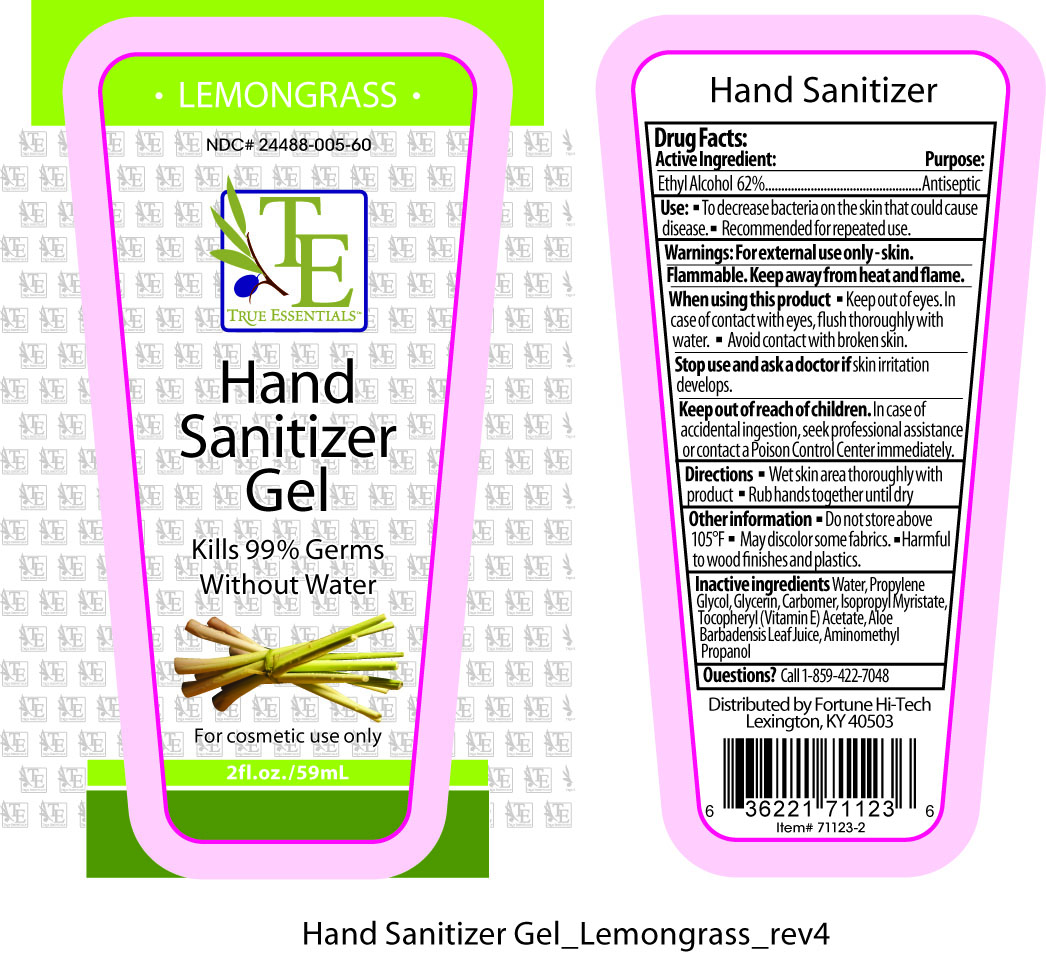 DRUG LABEL: True Essentials
NDC: 24488-005 | Form: GEL
Manufacturer: Fortune Hi-Tech
Category: otc | Type: HUMAN OTC DRUG LABEL
Date: 20110310

ACTIVE INGREDIENTS: ALCOHOL 36.58 mL/59 mL
INACTIVE INGREDIENTS: WATER; PROPYLENE GLYCOL; GLYCERIN; CARBOMER HOMOPOLYMER TYPE C ; ISOPROPYL MYRISTATE; ALPHA-TOCOPHEROL ACETATE; ALOE VERA LEAF; AMINOMETHYLPROPANOL

Drug Facts:

Active Ingredient:.............................Purpose:

Ethyl Alcohol 62%.............................Antiseptic

Use:

- To decrease bacteria on the skin that could cause disease.
- Recommended for repeated use.

Warning:

For external use only--skin.

Flammable.

Keep away from heat and flame.

When using this product:

- Keep out of eyes. In case of contact with eyes, flush thoroughly with water.
- Avoid contact with broken skin.

Stop use and ask a doctor if

skin irritation develops.

Keep out of reach of children.

In case of accidental ingestion, seek professional assistance or contact a Poison Control Center immediately.

Directions:

- Wet skin area thoroughly with product
- Rub hands until dry.

Other information:

- Do not store above 105°.
- May discolor some fabrics.
- Harmful to wood finishes and plastics.

Inactive ingredients:

Water, Propylene Glycol, Glycerin, Carbomer, Ispropyl Myristate, Tocopheryl (Vitamin E) Acetate, Aloe Barbadensis Leaf Juice, Aminomethyl Propanol

PACKAGE LABEL

Placeholder Text